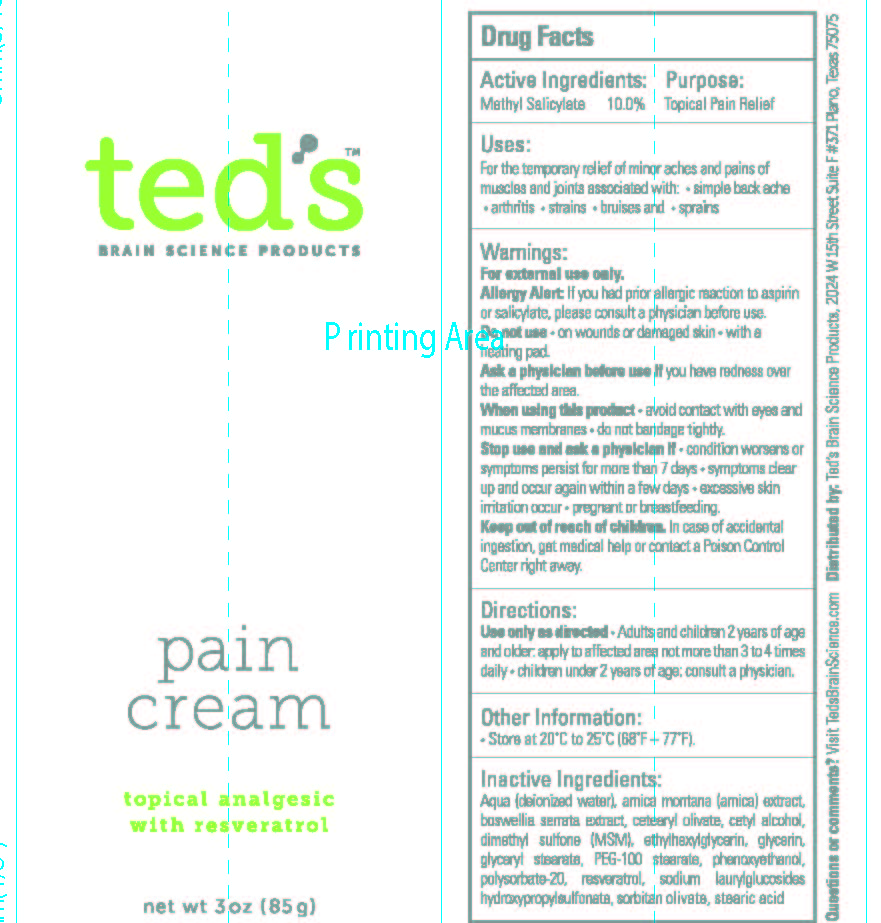 DRUG LABEL: teds topical pain cream
NDC: 58133-210 | Form: CREAM
Manufacturer: Cosmetic Specialty Labs, Inc.
Category: otc | Type: HUMAN OTC DRUG LABEL
Date: 20210111

ACTIVE INGREDIENTS: METHYL SALICYLATE 10 g/100 g
INACTIVE INGREDIENTS: CETEARYL OLIVATE; ETHYLHEXYLGLYCERIN; GLYCERIN; GLYCERYL STEARATE SE; PEG-100 STEARATE; PHENOXYETHANOL; POLYSORBATE 20; DIMETHYL SULFONE; ARNICA MONTANA FLOWER; CETYL ALCOHOL; WATER; RESVERATROL; SODIUM LAURYL GLYCOL CARBOXYLATE; SODIUM HYDROXYPROPYLSULFONATE LAURYLGLUCOSIDE-7 CROSSPOLYMER; SORBITAN OLIVATE; STEARIC ACID; BOSWELLIA SERRATA RESIN OIL

ted's Brain Science Products pain cream

Active ingredient

Methyl Salicylate - 10%

Purpose

Topical Pain Relief

Uses

For the temporarily relief of minor aches and pains of muscles and joints associated with: • simple back ache • arthritis • strains • bruises and • sprains

Warnings

For external use only

Allergy Alert

If you had prior allergic reaction to aspirin or salicylate, please consult a physician before use.

Do not use

- on wounds or damaged skin
- with a heating pad

Ask a physician before use if

- you have redness over the affected area

When using this product

• use only as directed • avoid contact with eyes and muscous membranes • do not bandage tightly

Stop use and ask a physician if

• condition worsens or symptoms persist for more than 7 days • symptoms clear up and occur again within a few days • excessive skin irritation occurs • pregnant or breast-feeding

Keep out of reach of the children

In case of accidental ingestion, get medical help or contact a Poison Control Center right away

Directions

Use only as directed

adults and children 2 years of age and older:

- apply to affected area not more than 3 or 4 times daily

children under 2 years of age: consult a physician

Other Information

Store at 20ºC to 25ºC (68ºF - 77ºF)

Inactive ingredients:

Aqua (deionized water), Arnica Montana (arnica) Extract, boswellia serrata extract, cetearyl olivate, cetyl alcohol, dimethyl sulfone (MSM), ethylhexylglycerin, glycerin, glyceryl stearate, PEG-100 stearate, phenoxyethanol, polysorbate 20, resveratrol, sodium laurylglucosides, hydroxypropylsulfonate, sorbitan olivate, stearic acid